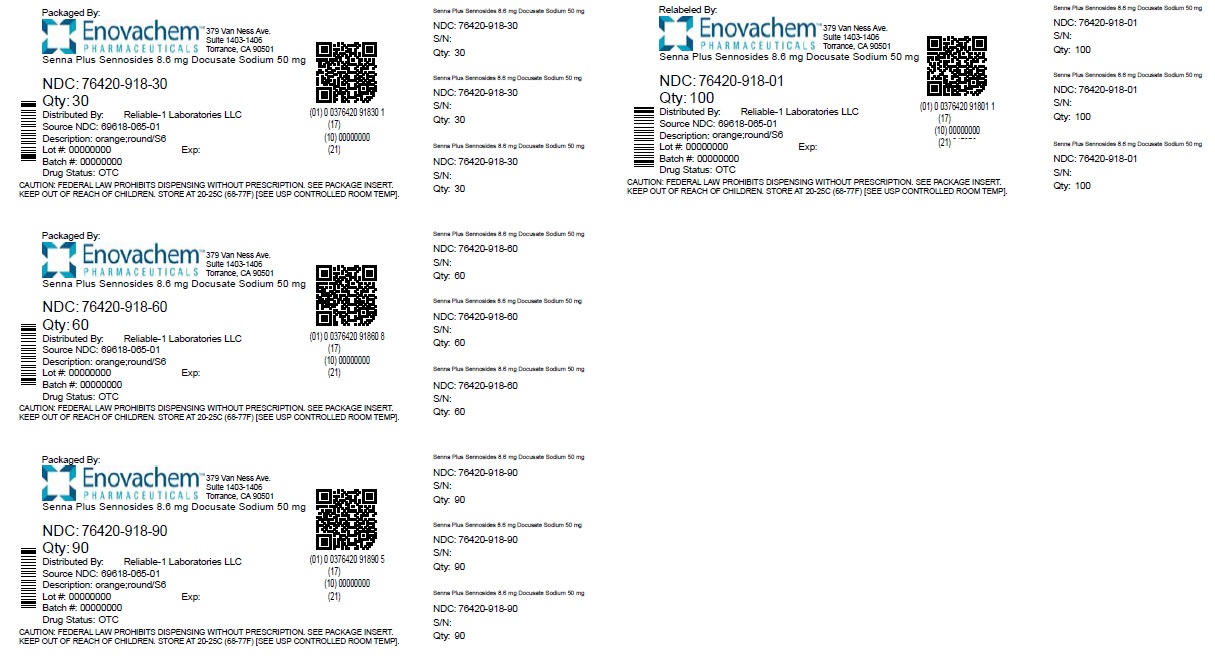 DRUG LABEL: Sennosides and Docusate Sodium
NDC: 76420-918 | Form: TABLET
Manufacturer: Asclemed USA, Inc.
Category: otc | Type: HUMAN OTC DRUG LABEL
Date: 20250208

ACTIVE INGREDIENTS: SENNOSIDES 8.6 mg/1 1; DOCUSATE SODIUM 50 mg/1 1
INACTIVE INGREDIENTS: TITANIUM DIOXIDE; SODIUM BENZOATE; D&C YELLOW NO. 10; MAGNESIUM STEARATE; CELLULOSE, MICROCRYSTALLINE; POLYETHYLENE GLYCOL 400; CROSCARMELLOSE SODIUM; FD&C YELLOW NO. 6; HYPROMELLOSES; SILICON DIOXIDE

Senna Plus

Drugs Facts

Active ingredient (in each tablet)

Docusate sodium 50 mg

Sennosides 8.6 mg

Purpose

Stool softener

Stimulant laxative

Uses

relieves occasional constipation (irregularity)

generally produces a bowel movement in 6 to 12 hours

Warnings

Do not use

this product if you are presently taking mineral oil, unless directed by a doctor

laxative products for longer than 1 week unless directed by a doctor

Warnings

Ask a doctor before use if you have

stomach pain

nausea

vomiting

noticed a sudden change in bowel habits that continues over a period of 2 weeks

Warnings

Stop use and ask a doctor ifyou have rectal bleeding or fail to have bowel movement after use of a laxative. These may indicate a serious condition.

Warnings

If pregnant or breast-feeding,ask a health professional before use.

Warnings

Keep out of reach of children.In case of overdose, get medical help or contact a Poison Control Center right away.

Directions

take preferably at bedtime or as directed by a doctor

do not exceed maximum dosage

age | starting dosage | maximun dosage
adults and children 12 years of age or older | 2 tablets once a day | 4 tablets twice a day
children 6 to under 12 years | 1 tablet once a day | 2 tablets twice a day
children 2 to under 6 years | 1/2 tablet once a day | 1 tablet twice a day
children under 2 years | ask a doctor | ask a doctor

Other information

each tablet contains: calcium 4 mg, sodium 8 mg

store at 25°C (77°F); excursions permitted between 15°-30°C (59°-86°F)

Inactive ingredients

colloidal silicon dioxide, croscarmellose sodium, D&C Yello #10 Aluminum Lake, FD&C Yellow #6 Aluminum Lake, hypromellose, magnesium stearate, microcrystalline cellulose, polyethylene glycol, sodium benzoate, titanium dioxide

Questions or comments?

Call 516-341-0666

8:30am-4:30pm ET, Mon-Fri

Repackaged and Relabeled by:
Enovachem PHARMACEUTICALS
Torrance, CA 90501